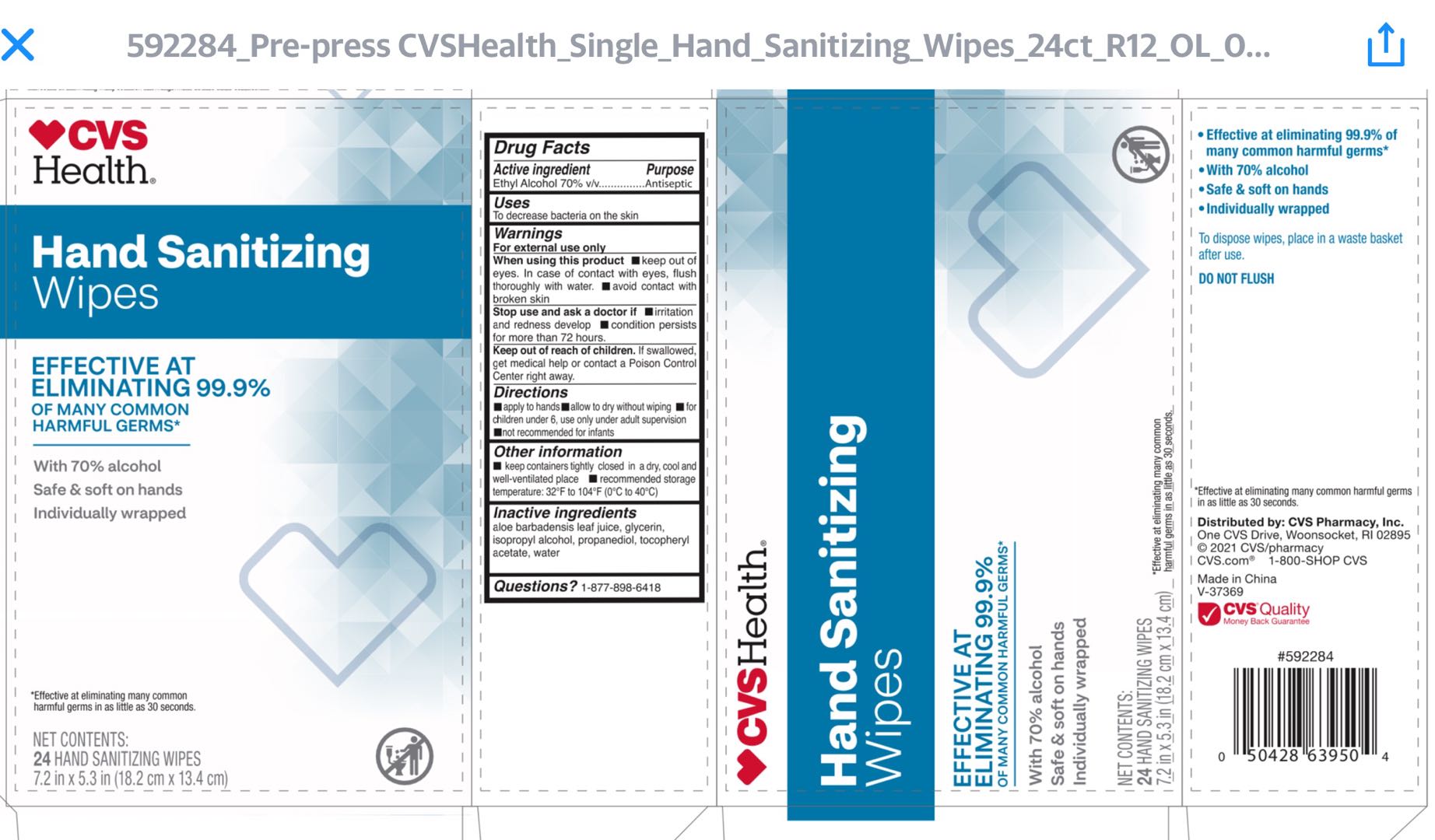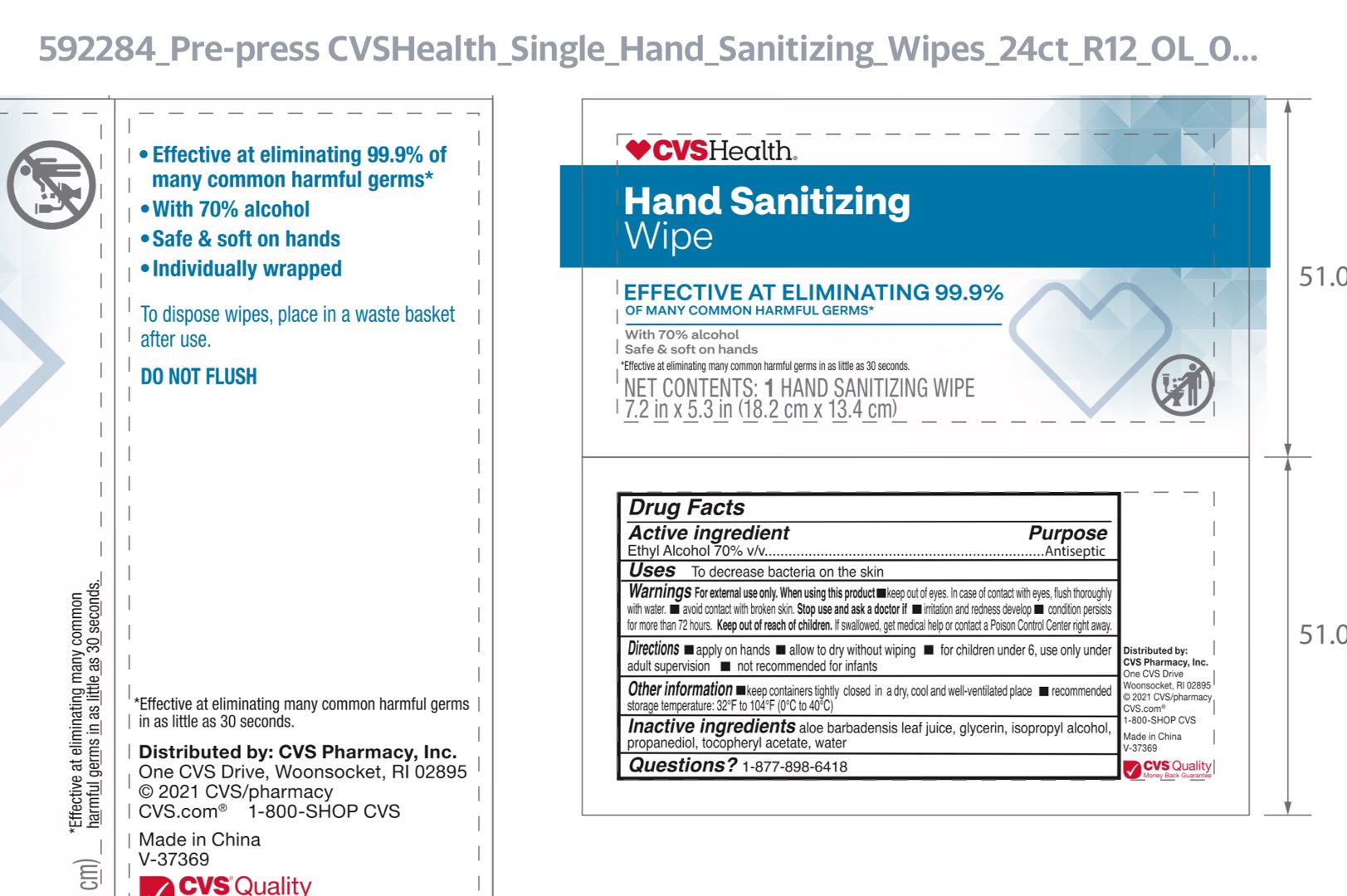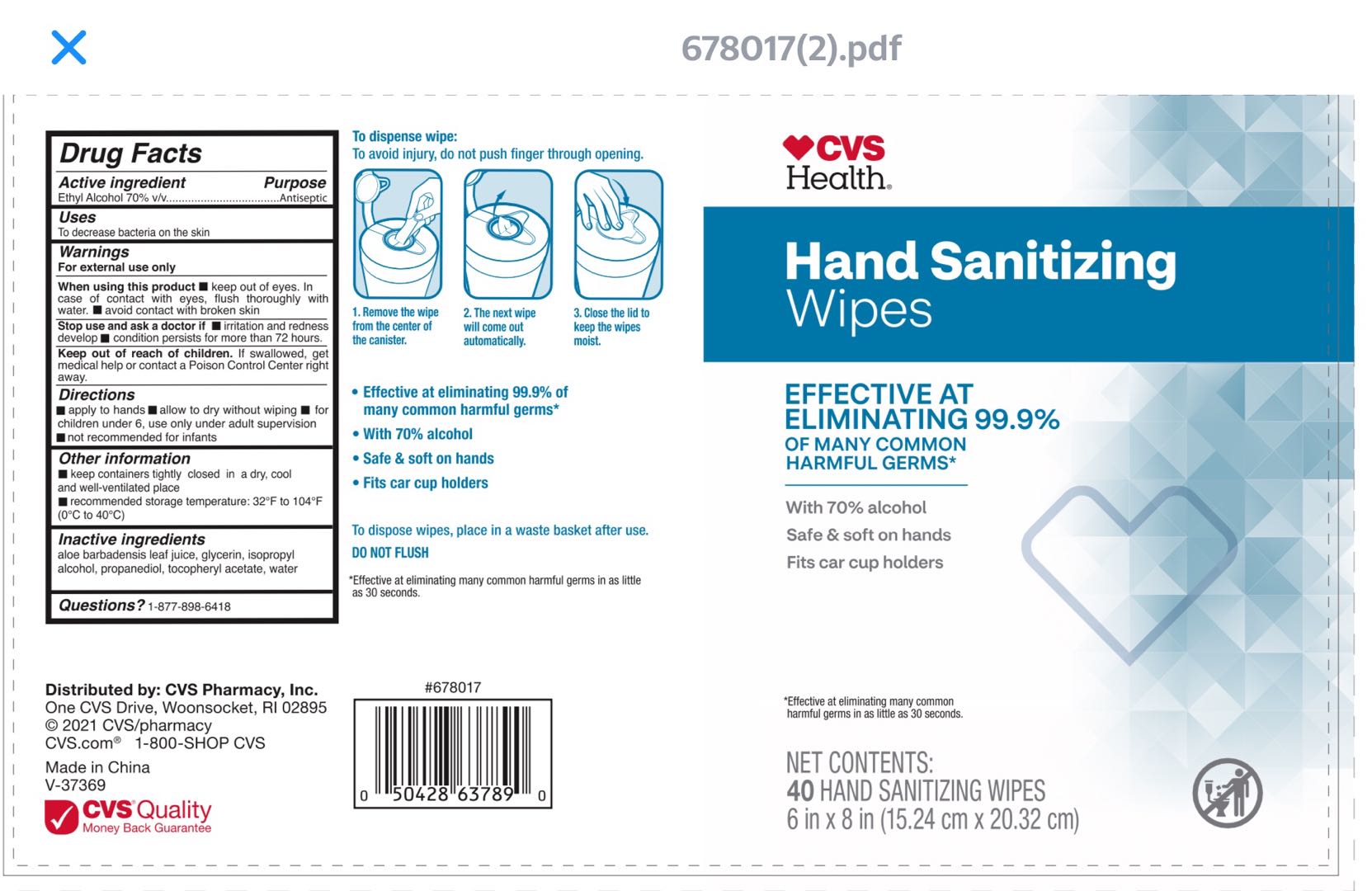 DRUG LABEL: CVS Health Hand Sanitizing Wipes
NDC: 51316-002 | Form: SOLUTION
Manufacturer: CVS PHARMACY, INC
Category: otc | Type: HUMAN OTC DRUG LABEL
Date: 20210527

ACTIVE INGREDIENTS: ALCOHOL 70 mL/100 mL
INACTIVE INGREDIENTS: WATER; ALOE VERA LEAF; GLYCERIN; ISOPROPYL ALCOHOL; PROPANEDIOL; .ALPHA.-TOCOPHEROL ACETATE

51316-002 CVS SKU 678017, 592284

Active Ingredient

Ethyl Alcohol 70% v/v

Purpose

Antiseptic

Use

To decrease bacteria on the skin

Warnings

For external use only

When using this product

- keep out of eyes. In case of contact with eyes, flush thoroughly with water.
- Avoid contact with broken skin

Stop use and ask a doctor if

- irritation and redness develop
- condition persists for more than 72 hours

Keep out of reach of children. If swallowed, get medical help or contact a Poison Control Center right away.

Directions

- Apply to hands
- Allow to dry without wiping
- For children under 6, use only under adult supervision
- Not recommended for infants

Other information

- Keep containers tightly closed in a dry, cool and well ventilated place
- Recommended storage temperature: 32F to 104F (0C to 40C)

Inactive ingredients

Aloe Barbadensis Leaf Juice, Glycerin, Isopropyl Alcohol, Propanediol, Tocopheryl Acetate, Water